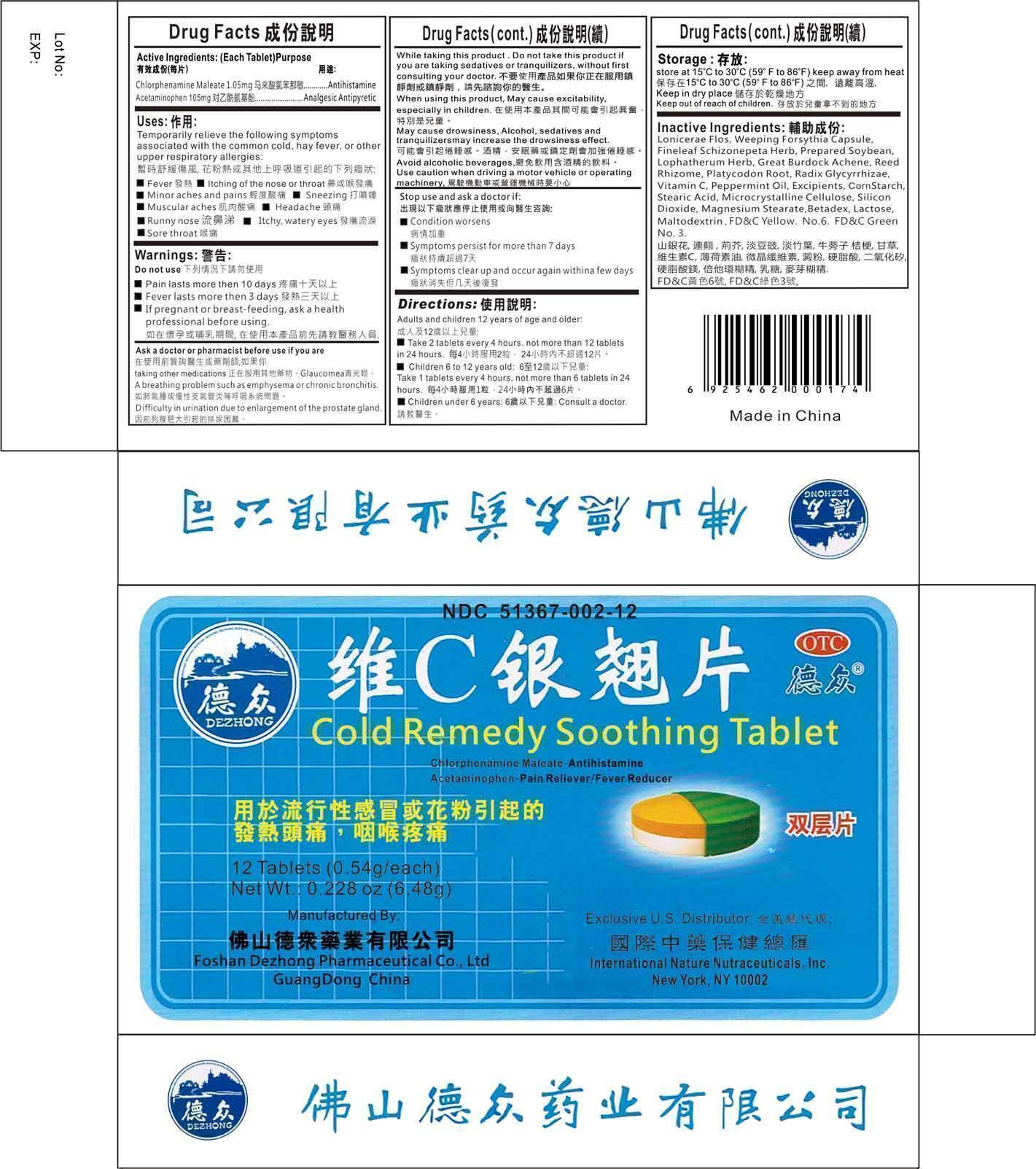 DRUG LABEL: Cold Remedy Soothing
NDC: 51367-002 | Form: TABLET
Manufacturer: International Nature Nutraceuticals
Category: otc | Type: HUMAN OTC DRUG LABEL
Date: 20120801

ACTIVE INGREDIENTS: CHLORPHENIRAMINE MALEATE 1.05 mg/1 1; ACETAMINOPHEN 105 mg/1 1
INACTIVE INGREDIENTS: LONICERA CONFUSA WHOLE; FORSYTHIA SUSPENSA WHOLE; SCHIZONEPETA TENUIFOLIA FLOWERING TOP; SOYBEAN; LOPHATHERUM GRACILE LEAF; ARCTIUM LAPPA FRUIT; PHRAGMITES AUSTRALIS ROOT; PLATYCODON GRANDIFLORUM ROOT; GLYCYRRHIZA URALENSIS; ASCORBIC ACID; PEPPERMINT OIL; MODIFIED CORN STARCH (1-OCTENYL SUCCINIC ANHYDRIDE); STEARIC ACID; CELLULOSE, MICROCRYSTALLINE; SILICON DIOXIDE; MAGNESIUM STEARATE; BETADEX; LACTOSE; MALTODEXTRIN; FD&C YELLOW NO. 6; FD&C GREEN NO. 3

Active Ingredients

Chlorphenamine Maleate 1.05 mg

Acetaminophen 105 mg

Uses

Temporarily relieve the following symptoms associated with the common cold, hay fever, or other upper respiratory allergies:

- Fever
- Itiching of the nose or throat
- Minor aches and pains
- Sneezing
- Muscle aches
- Headache
- Runny nose
- Itchy eyes

Warnings

Do Not Use:

- Pain lasts more than 10 days
- Fever lasts more than 3 days
- If pregnant or breast-feeding, ask a health professional before using

Ask a doctor or pharmacist before use if you are

- Taking other medications
- Have glaucomea
- A breathing problem such as emphysema or chronic bronchitis
- Difficulty in urination due to enlargement of the prostate gland

While taking this product

Do not use this product if you are taking sedatives or tranquilizers, without first consulting your doctor.

When using this product, may cause excitability, especially in children

May cause drowsiness. Alcohol, sedatives, and tranquilizers may increase the drowsiness effect.

Avoid alcoholic beverages

Use caution when driving a motor vehicle or operating machinery.

Stop use and doctor if

- Condition worsens
- Symptoms persit for more than 7 days
- Symptoms clear up and occur again within a few days

Directions

Adults and children 12 years of age and older

- Take 2 tablets every 4 hours, not to exceed more than 12 tablets in 24 hours

Children ages 6 to 12 years old

- Take 1 tablet every 4 hours, not to exceed more than 6 tablets in 24 hours

Children under 6 years of age

- Consult a doctor

Storage

Store at 15°C to 30°C (59°F to 86°F)

Keep away from heat

Store in a dry place

Inactive Ingredients

Lonicerae Flos, Weeping Forsythia Capsule, Fineleaf Schizonepeta Herb, Prepared Soybean, Lophatherum Herb, Great Burdock Achene, Reed Rhizome, Platycodon Root, Radix Glycyrrhizae, Vitamin C, Peppermint Oil.

Excipients:

Corn Starch, Stearic Acid, Microcrystalline Cellulose, Silicon Dioxide, Magnesium Stearate, Betadex, Lactose, Maltodextrin, FD&C Yellow No. 6, FD&C Green No. 3